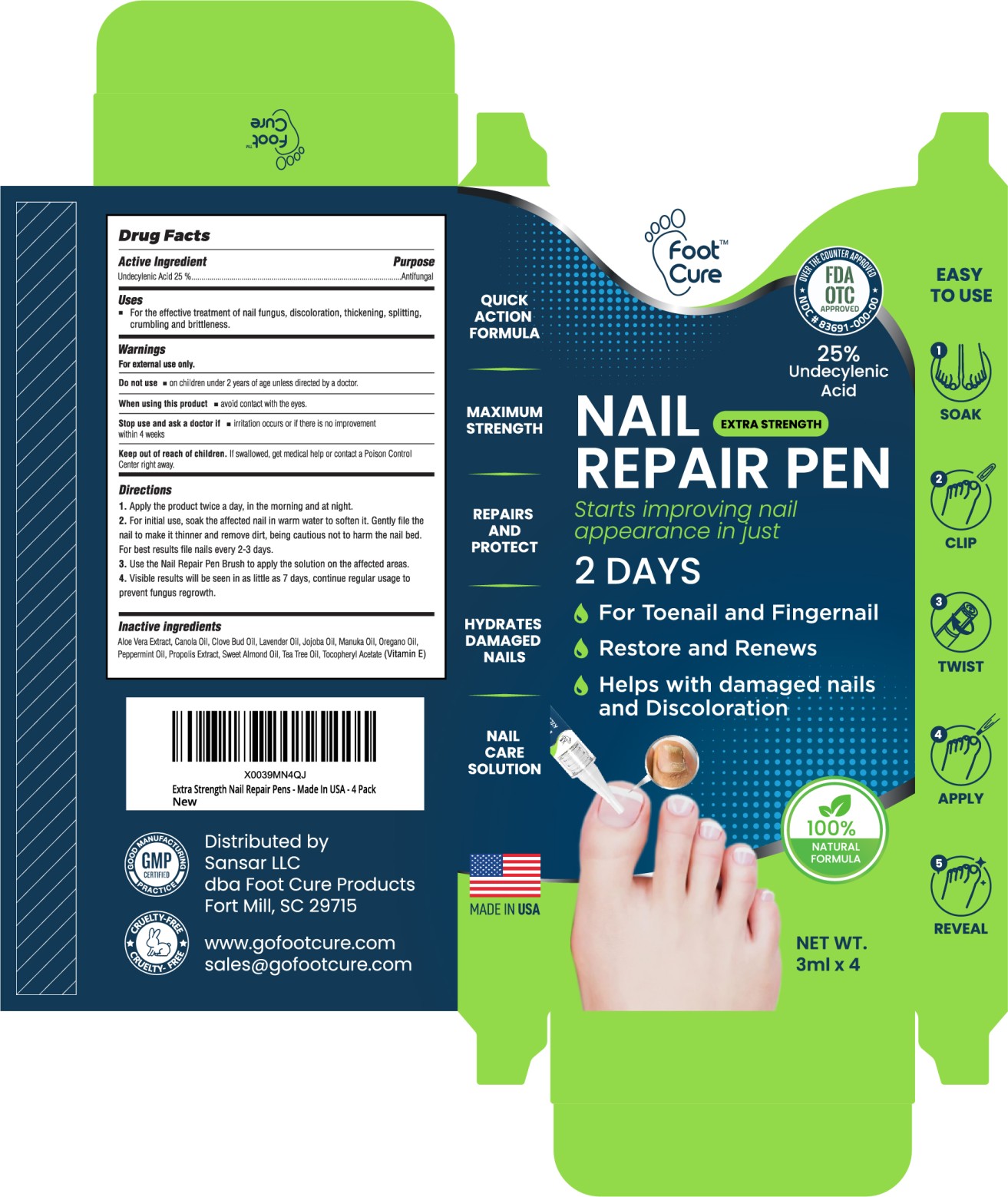 DRUG LABEL: Foot Cure Nail Repair Pen
NDC: 83691-002 | Form: SOLUTION
Manufacturer: Sansar LLC
Category: otc | Type: HUMAN OTC DRUG LABEL
Date: 20240725

ACTIVE INGREDIENTS: UNDECYLENIC ACID 2.5 g/100 g
INACTIVE INGREDIENTS: PROPOLIS WAX; OREGANO LEAF OIL; .ALPHA.-TOCOPHEROL ACETATE; LAVENDER OIL; ALMOND OIL; CLOVE OIL; PEPPERMINT OIL; JOJOBA OIL; MANUKA OIL; CANOLA OIL; TEA TREE OIL; ALOE VERA WHOLE

ACTIVE INGREDIENT

Undecylenic Acid 25%...........................Antifungal

INTENDED USE OF THE DEVICE

For the effective treatment of nail fungus, discolartion, thickening, splitting, crumbling and brittleness.

WARNINGS

For external use only.

WARNINGS AND PRECAUTIONS

Apply the product twice a day, in the morning and at night.

INACTIVE INGREDIENT

Alo Vera Extract, Canola Oil, Clove Bud Oil, Lavender Oil, Jojoba Oil, Manuka Oil, Oregano Oil, Peppermint Oil, Propolis Extract, Sweet Almond Oil, Tea Tree Oil, Tocopheryl Acetate (Vitamin E)

DOSAGE AND ADMINISTRATION

3ml X 4 Pen

INDICATIONS AND USAGE

Use the Nail repair pen brush to apply the solution on the affected areas.

Keep out of reach of children. If swallowed, get medical help or contact a Poison Control centre right away.

PURPOSE

For the effective treatment of nail fungus, discolartion, thickening, splitting, crumbling and brittleness.